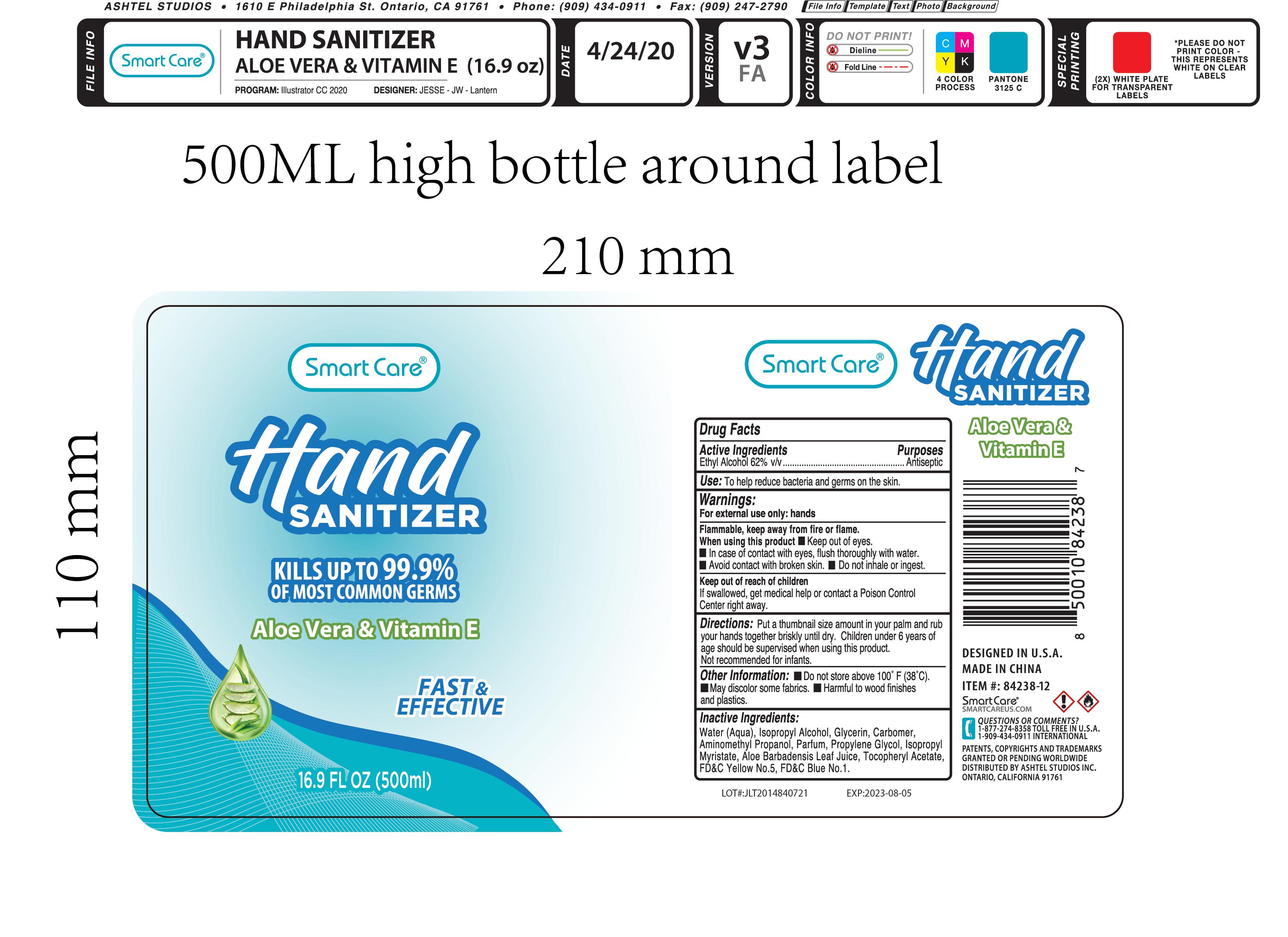 DRUG LABEL: Smart Care Hand Sanitizer 16.9oz
NDC: 54860-411 | Form: LIQUID
Manufacturer: Shenzhen Lantern Science Co.,Ltd
Category: otc | Type: HUMAN OTC DRUG LABEL
Date: 20230515

ACTIVE INGREDIENTS: ALCOHOL 62 mL/100 mL
INACTIVE INGREDIENTS: ALOE VERA LEAF 0.1 mL/100 mL; ALOE 0.15 mL/100 mL; ISOPROPYL MYRISTATE 0.001 mL/100 mL; CARBOMER 940 0.26 mL/100 mL; WATER 36.307916 mL/100 mL; ISOPROPYL ALCOHOL 0.5 mL/100 mL; FD&C YELLOW NO. 5 0.00006 mL/100 mL; AMINOMETHYLPROPANOL 0.08 mL/100 mL; FD&C BLUE NO. 1 0.000024 mL/100 mL; GLYCERIN 0.5 mL/100 mL; PROPYLENE GLYCOL 0.1 mL/100 mL; .ALPHA.-TOCOPHEROL ACETATE 0.001 mL/100 mL

Smart Care Hand Sanitizer 16.9oz

Drug Facts

Active Ingredient

Active Ingredients Purpose

Ethyl Alcohol 62% Antiseptic

purpose

antiseptic

DOSAGE AND ADMINISTRATION

Recommended for repeated use.

use anywhere without water.

Warning

For external use only:hands

Flammable,keep away from fire or flame.

When using this product

keep out of eyes.

In case of contact with eyes,flush thoroughly with water.

Avoid contact with broken skin.

Do not inhale or ingest.

Keep out of reach of children.

If swallowed,get medical help or contact a Poison Control Center right away.

WARNINGS AND PRECAUTIONS

For external use only.

Flammable, keep away from heat and flame.

STOP USE

Discontinue if skin becomes irritated and ask a doctor .

Keep out of reach of children. In case of accidental ingestion, seek professional assistance or contact a poson control center immediately.

Non-Medicinal

Alcohol，Aqua(water)，Isopropyl Alcohol，Glycerin，Carbomer，Aminomethyl Propanol，Parfum，Propylene Glycol，ISOPROPYL MYRISTATE，ALOE BARBADENSIS LEAF JUICE，Tocopheryl Acetate，FD&C Yellow No.5(Tartrazine),FD&C Blue No.1.

Directions

Put a thumbnail size amount in your palm and rub your hands together briskly until dry.Children under 6 years of age should be supervised when using SMART CARE®HAND SANITIZER.Not recommended for infants.

When using this product

keep out of eyes. In case of contact with eyes, flush thoroughly with water.

Do not inhale or ingest.

Avoid contact with broken skin.

Other information

Do not store above 105F.

May discolor some fabrics.

Harmful to wood finishes and plastics.

OTHER SAFETY INFORMATION

Do not store above100℉（38℃）

May discolor some fabrics.

Harmful to wood finishes and plastics.

Packaging